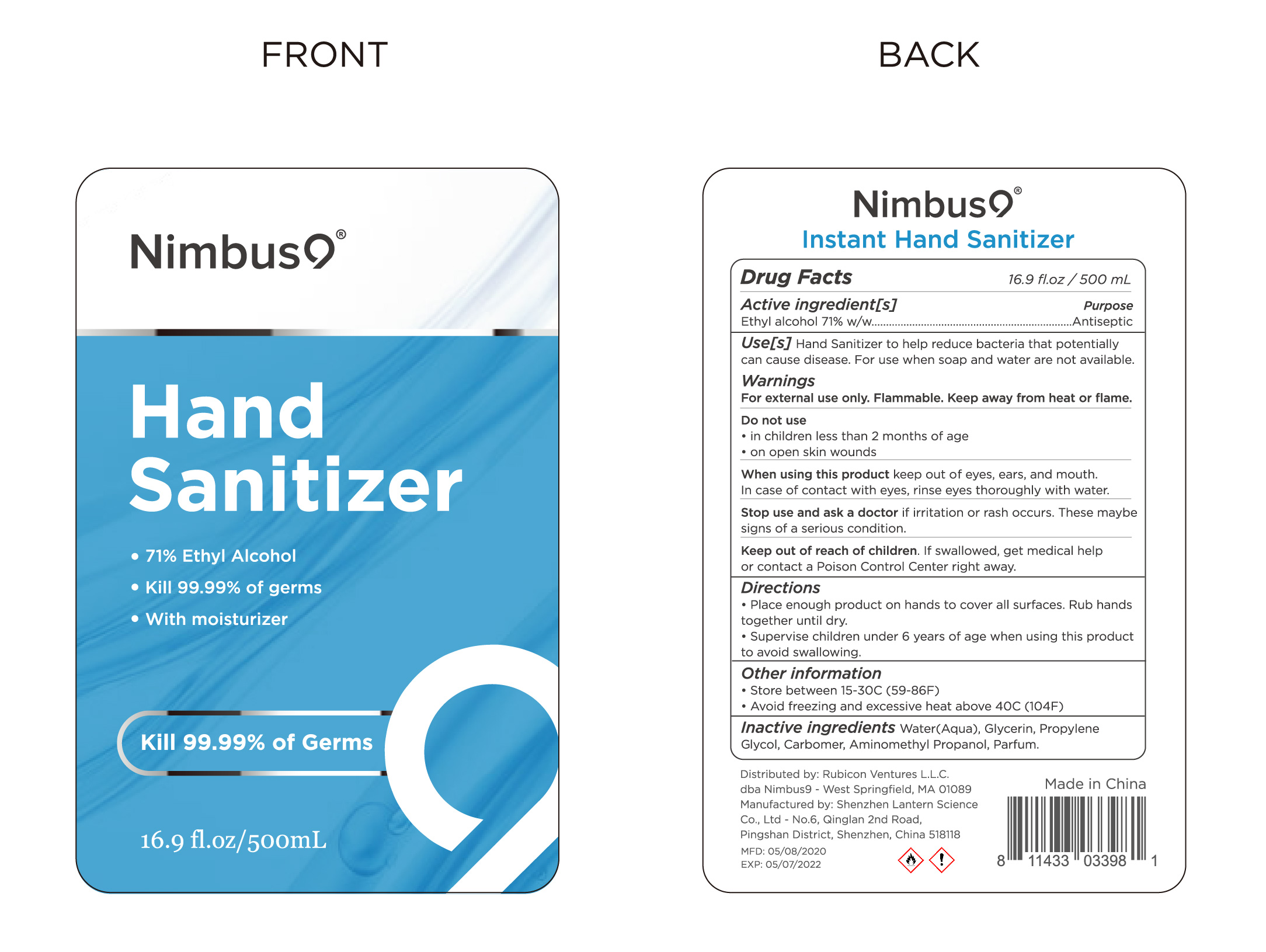 DRUG LABEL: Nimbus9  hand sanitizer 500ml

NDC: 54860-279 | Form: LIQUID
Manufacturer: Shenzhen Lantern Scicence Co.,Ltd.
Category: otc | Type: HUMAN OTC DRUG LABEL
Date: 20211227

ACTIVE INGREDIENTS: ALCOHOL 71 g/100 g
INACTIVE INGREDIENTS: CARBOMER 940 0.35 g/100 g; PROPYLENE GLYCOL 0.01 g/100 g; AMINOMETHYLPROPANOL 0.11 g/100 g; WATER 28.42 g/100 g; GLYCERIN 0.01 g/100 g; LEMON 0.1 g/100 g

Lantern-Nimbus9 hand sanitizer 500ml

Active Ingredient

Active Ingredient Purpose

Ethyl Alcohol 71%（w/w） Antiseptic

USE

Hand sanitizer to help reduce bacteria that potentially can cause disease.For use when soap and water are not available.

DOSAGE AND ADMINISTRATION

Recommended for repeated use.

use anywhere without water.

Warning

For external use only.Flammable.Keep away from heat or flame.

WARNINGS AND PRECAUTIONS

For external use only.

Flammable, keep away from heat and flame.

STOP USE

Discontinue if skin becomes irritated and ask a doctor .

Keep out of reach of children. In case of accidental ingestion, seek professional assistance or contact a poson control center immediately.

Inactive ingredients

Water, Glycerin,propylene Glycol,carbomer,Aminomethyl propanol,Parfum.

Directions

Place enough product on hands to cover all surfaces,Rub hands together until dry.

Supervise children under 6 years of age when using this product to avoid swallowing.

When using this product

keep out of eyes. In case of contact with eyes, flush thoroughly with water.

Do not inhale or ingest.

Avoid contact with broken skin.

Other information

Do not store above 105F.

May discolor some fabrics.

Harmful to wood finishes and plastics.

Do not use

in children less than 2 months of age

on open skin wounds or burns

When using this product

keep out of eyes,ears,and mouth.In case of contact with eyes,rinse eyes thoroughly with water.

Stop use and ask a doctor

if irritation or rash occurs,these maybe signs of a serious condition.

keep out of reach of children

If swallowed,get medical help or contact a Poison Control Center right away.

Other information

Store between 15-30C（59-86F）

Avoid freezing and excessive heat above the 40℃（104F）